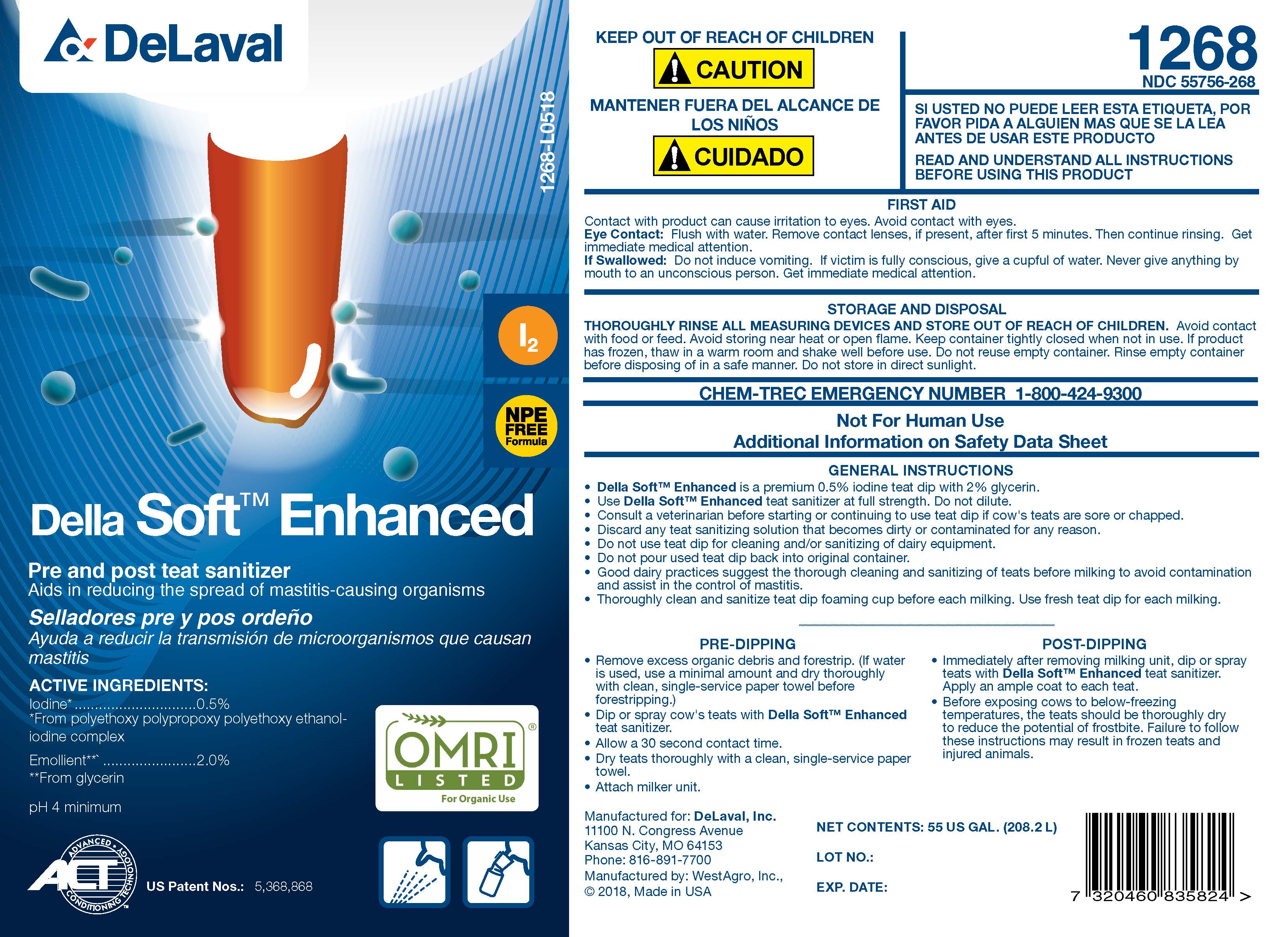 DRUG LABEL: Della Soft Enhanced
NDC: 55756-268 | Form: SOLUTION
Manufacturer: DeLaval
Category: animal | Type: OTC ANIMAL DRUG LABEL
Date: 20230906

ACTIVE INGREDIENTS: IODINE 5.1 g/1 L

DeLaval Della Soft Enhanced

Pre and post teat sanitizer

Selladores pre y pos ordeno

ACTIVE INGREDIENTS:

Iodine .......................................... 0.5%
from polyethoxy polypropoxy polyethoxy ethanol-iodine complex
pH 4 minimum

US Patent Nos.: 5,368,868

KEEP OUT OF REACH OF CHILDREN

! CAUTION

MANTENER FUERA DEL ALCANCE DE LOS NINOS

! CUIDADO

1268

NDC 55756-268

SI USTED NO PUEDE LEER ESTA ETIQUETA, POR FAVOR PIDA A ALGUIEN MAS QUE SE LA LEA ANTES DE USAR ESTE PRODUCTO

READ AND UNDERSTAND ALL INSTRUCTIONS BEFORE USING THIS PRODUCT

FIRST AID

Contact with product can cause irritation to eyes. Avoid contact with eyes.
Eye Contact: Flush with water. Remove contact lenses, if present, after first 5 minutes. Then continue rinsing. Get immediate medical attention.
If Swallowed: Do not induce vomiting. If victim is fully conscious, give a cupful of water. Never give anything by mouth to an unconscious person. Get immediate medical attention.

STORAGE AND DISPOSAL

THOROUGHLY RINSE ALL MEASURING DEVICES AND STORE OUT OF REACH OF CHILDREN. Avoid contact with food or feed. Avoid storing near heat or open flame. Keep container tightly closed when not in use. If product has frozen, thaw in a warm room and shake well before use. Do not reuse empty container. Rinse empty container before disposing of in a safe manner. Do not store in direct sunlight.

CHEM-TREC EMERGENCY NUMBER 1-800-424-9300

Not For Human Use

Additional Information on Material Safety Data Sheet

INDICATIONS AND USAGE

GENERAL INSTRUCTIONS

- Della Soft Enhanced is a premium 0.5% iodine teat dip with 2% emollient.
- Use Della Soft Enhanced teat sanitizer at full strength. Do not dilute.
- Consult a veterinarian before starting or continuing to use teat dip if cow's teats are sore or chapped.
- Discard any teat sanitizing solution that becomes dirty or contaminated for any reason.
- Do not use teat dip for cleaning and/or sanitizing of dairy equipment.
- Do not pour used teat dip back into original container.
- Good dairy practices suggest the thorough cleaning and sanitizing of teats before milking to avoid contamination and assist in the control of mastitis.
- Thoroughly clean and sanitize teat dip foaming cup before each milking. Use fresh teat dip for each milking.

PRE-DIPPING

- Remove excess organic debris and forestrip. (If water is used, use a minimal amount and dry thoroughly with a clean, single-service paper towel before forestripping.)
- Dip or spray cow's teats with Della Soft Enhanced teat sanitizer.
- Allow a 30 second contact time.
- Dry teats thoroughly with a clean, single-service paper towel.
- Attach milker unit.

POST-DIPPING

- Immediately after removing milking unit, dip or spray teats with Della Soft Enhanced teat sanitizer. Apply an ample coat to each teat.

- Before exposing cows to below-freezing temperatures, the teats should be thoroughly dry to reduce the potential of frostbite. Failure to follow these instruction may result in frozen teats and injured animals.

Manufactured for: DeLaval, Inc.
11100 N. Congress Avenue
Kansas City, MO 64153
Phone: 816-891-7700
Manufactured by: WestAgro, Inc.
©2018, Made in USA

NET CONTENTS:

LOT NO.:

EXP. DATE: